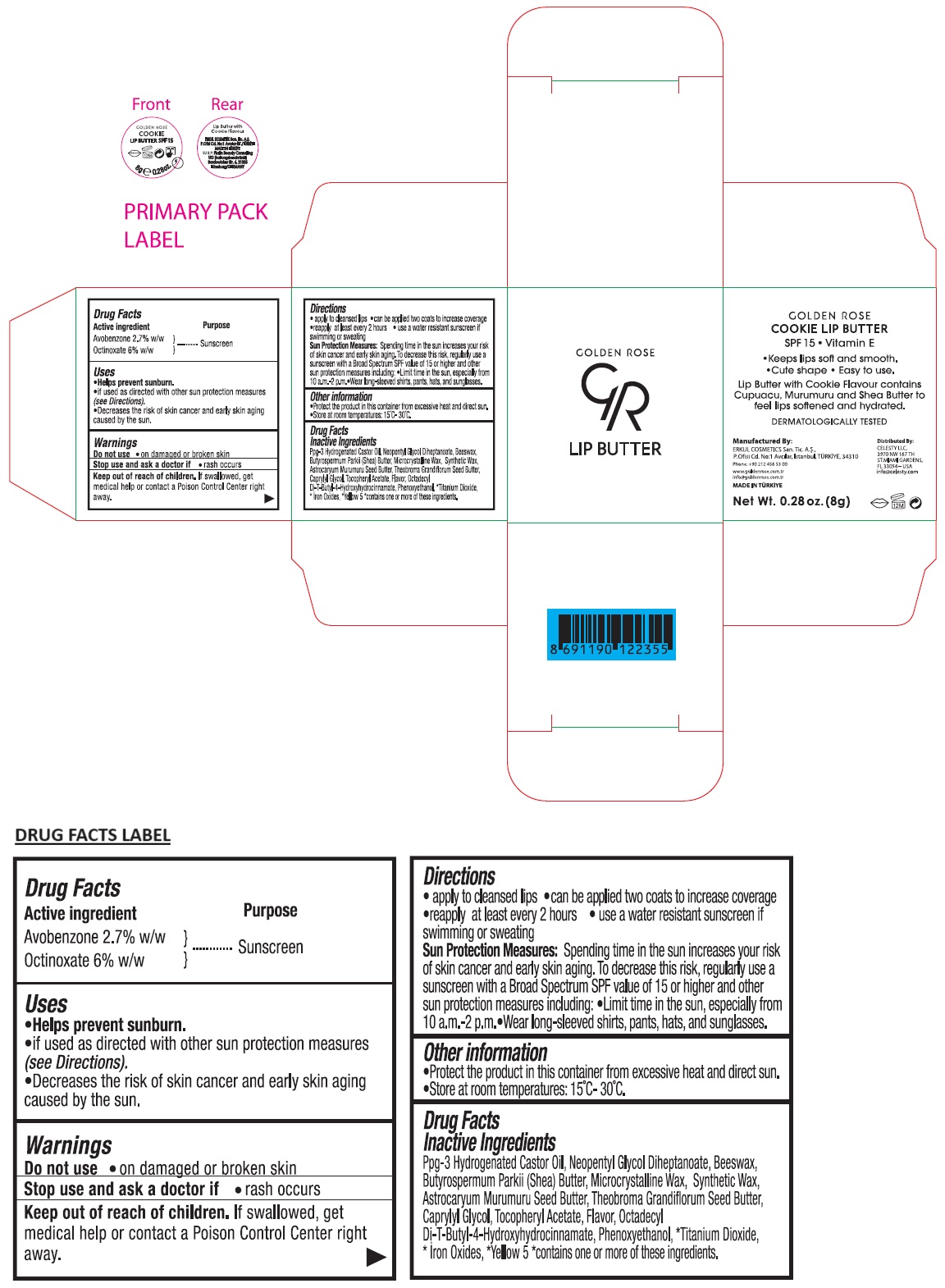 DRUG LABEL: GR LIP BUTTER COOKIE SPF 15
NDC: 82715-119 | Form: LIPSTICK
Manufacturer: ERKUL KOZMETIK SANAYI VE TICARET ANONIM SIRKETI
Category: otc | Type: HUMAN OTC DRUG LABEL
Date: 20250808

ACTIVE INGREDIENTS: AVOBENZONE 2.7 g/100 g; OCTINOXATE 6 g/100 g
INACTIVE INGREDIENTS: HYDROGENATED CASTOR OIL; NEOPENTYL GLYCOL DIHEPTANOATE; YELLOW WAX; SHEA BUTTER; MICROCRYSTALLINE WAX; PARAFFIN; ASTROCARYUM MURUMURU SEED BUTTER; THEOBROMA GRANDIFLORUM SEED BUTTER; CAPRYLYL GLYCOL; .ALPHA.-TOCOPHEROL ACETATE; OCTADECYL DI-TERT-BUTYL-4-HYDROXYHYDROCINNAMATE; PHENOXYETHANOL; TITANIUM DIOXIDE; FERRIC OXIDE RED; FERRIC OXIDE YELLOW; FERROSOFERRIC OXIDE; FD&C YELLOW NO. 5

GR LIP BUTTER COOKIE SPF 15

Active ingredient

Avobenzone 2.7% w/w
Octinoxate 6% w/w

Purpose

Sunscreen

Uses

• Helps prevent sunburn.
• if used as directed with other sun protection measures (see Directions).
• Decreases the risk of skin cancer and early skin aging caused by the sun.

Warnings

Do not use • on damaged or broken skin

Stop use and ask a doctor if • rash occurs

Keep out of reach of children. If swallowed, get medical help or contact a Poison Control Center right away.

Directions

• apply to cleansed lips • can be applied two coats to increase coverage • reapply at least every 2 hours • use a water resistant sunscreen if swimming or sweating
Sun Protection Measures: Spending time in the sun increases your risk of skin cancer and early skin aging. To decrease this risk, regularly use a sunscreen with a Broad Spectrum SPF value of 15 or higher and other sun protection measures including: • Limit time in the sun, especially from 10 a.m.-2 p.m. • Wear long-sleeved shirts, pants, hats, and sunglasses.

Other information

• Protect the product in this container from excessive heat and direct sun.
• Store at room temperatures: 15°C- 30°C.

Inactive Ingredients

Ppg-3 Hydrogenated Castor Oil, Neopentyl Glycol Diheptanoate, Beeswax, Butyrospermum Parkii (Shea) Butter, Microcrystalline Wax, Synthetic Wax, Astrocaryum Murumuru Seed Butter, Theobroma Grandiflorum Seed Butter, Caprylyl Glycol, Tocopheryl Acetate, Flavor, Octadecyl Di-T-Butyl-4-Hydroxyhydrocinnamate, Phenoxyethanol, *Titanium Dioxide, *Iron Oxides,*Yellow 5 *contains one or more of these ingredients.

• Vitamin E

• Keeps lips soft and smooth.

• Cute shape

• Easy to use.

Lip Butter with Cookie Flavour contains Cupuacu, Murumuru and Shea Butter to feel lips softened and hydrated.

DERMATOLOGICALLY TESTED

Manufactured By:
ERKUL COSMETICS San. Tic. A.S.,
P.Ofisi Cd. No:1 Avcılar, Istanbul, TURKIYE, 34310

Phone: +90 212 456 53 00

www.goldenrose.com.tr
info@goldenrose.com.tr

MADE IN TURKIYE

Distributed By:
CELESTY LLC,
3970 NW 167 TH
ST.MIAMI GARDENS,
FL 33054 - USA
info@celesty.com

EU R.P: Platin Beauty Consulting UG (haftungsbeschränkt)
Bardowicker Str. 6, 21335
Lüneburg/GERMANY